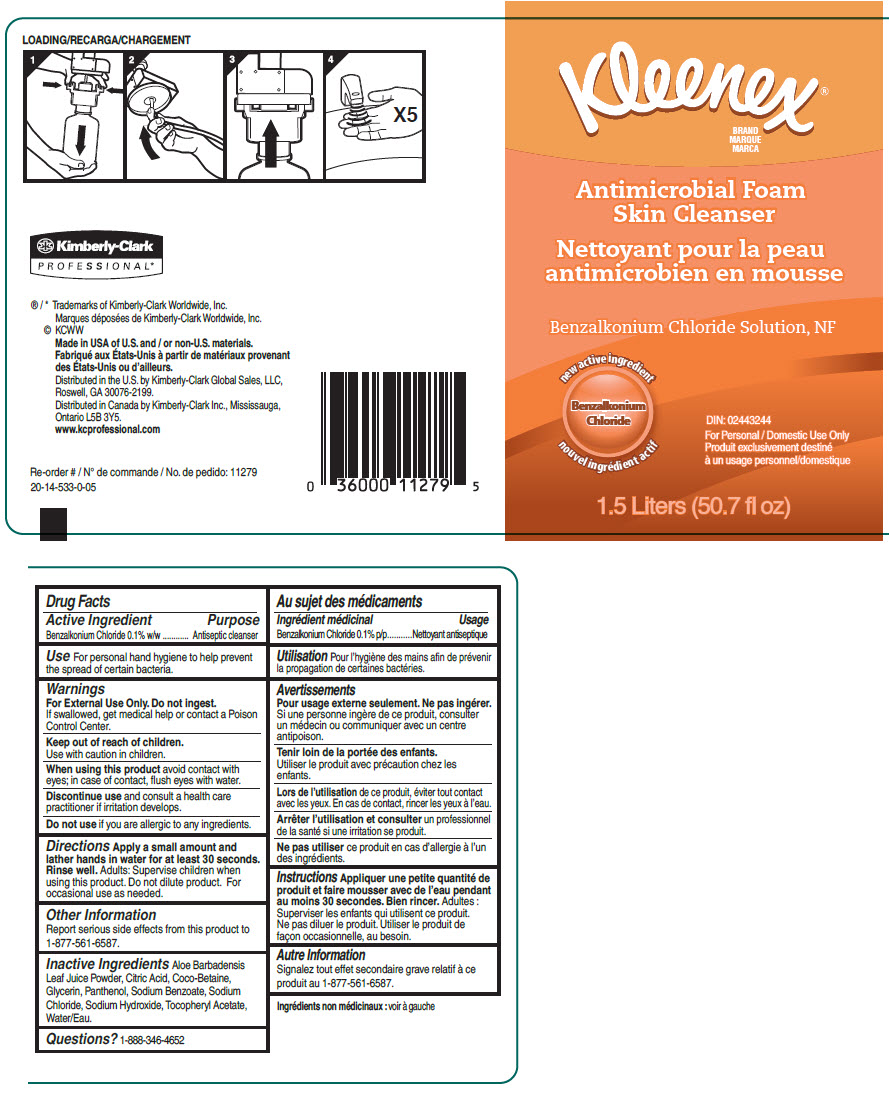 DRUG LABEL: KLEENEX Antimicrobial Foam Skin Cleanser
NDC: 55118-700 | Form: SOLUTION
Manufacturer: Kimberly-Clark
Category: otc | Type: HUMAN OTC DRUG LABEL
Date: 20191016

ACTIVE INGREDIENTS: Benzalkonium Chloride 1 mg/1000 mL
INACTIVE INGREDIENTS: Water; Coco-Betaine; Glycerin; Sodium Chloride; Sodium Benzoate; Citric Acid Monohydrate; Aloe; Panthenol; .Alpha.-Tocopherol Acetate; Sodium Hydroxide

KLEENEX® Antimicrobial Foam Skin Cleanser

Drug Facts

Active Ingredient

Benzalkonium Chloride 0.1% w/w

Purpose

Antiseptic cleanser

Use

For personal hand hygiene to help prevent the spread of certain bacteria.

Warnings

For External Use Only. Do not ingest

Use with caution in children

When using this product avoid contact with eyes; in case of contact, flush eyes with water.

STOP USE

Discontinue use and consult a health care practitioner if irritation develops

Keep out of reach of children. If swallowed, get medical help or contact a Poison Control Center.

Do not use if you are allergic to any ingredients.

Directions

Apply a small amount and lather hands in water for at least 30 seconds. Rinse well. Adults: Supervise children when using this product. Do not dilute product. For occasional use as needed.

Other Information

Report serious side effects from this product to 1-877-561-6587.

Inactive Ingredients

Aloe Barbadensis Leaf Juice Powder, Citric Acid, Coco-Betaine, Glycerin, Panthenol, Sodium Benzoate, Sodium Chloride, Sodium Hydroxide, Tocopheryl Acetate, Water.

Questions?

1-888-346-4652

Distributed in the U.S. by Kimberly-Clark Global Sales, LLC,
Roswell, GA 30076-2199.

Distributed in Canada by Kimberly-Clark Inc., Mississauga,
Ontario L5B 3Y5.

PRINCIPAL DISPLAY PANEL - 50.7 fl oz Bottle Label

Kleenex®
BRAND

Antimicrobial Foam
Skin Cleanser

Benzalkonium Chloride Solution, NF

new active ingredient
Benzalkonium
Chloride

DIN: 02443244
For Personal / Domestic Use Only

1.5 Liters (50.7 fl oz)